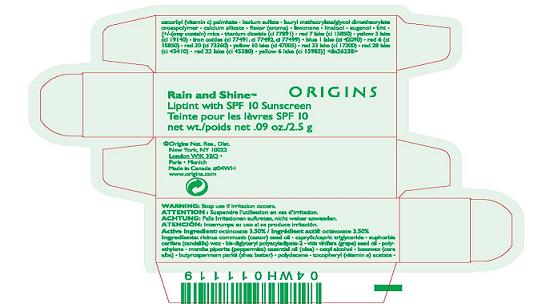 DRUG LABEL: RAIN AND SHINE LIPTINT
NDC: 59427-728 | Form: LIPSTICK
Manufacturer: ORIGINS NATURAL RESOURCES INC
Category: otc | Type: HUMAN OTC DRUG LABEL
Date: 20100413

ACTIVE INGREDIENTS: OCTINOXATE 3.5 g/100 g

ACTIVE INGREDIENT: OCTINOXATE 3.5%

WARNINGS

WARNING: STOP USE IF IRRITATION OCCURS

PACKAGE LABEL

PRINCIPAL DISPLAY PANEL

ORIGINS

RAIN AND SHINE

LIP TINT WITH SPF 10 SUNSCREEN

NET WT 0.9 OZ / 2.5 GM

ORIGINS NAT. RES. DISTR.

NEW YORK, NY 10022